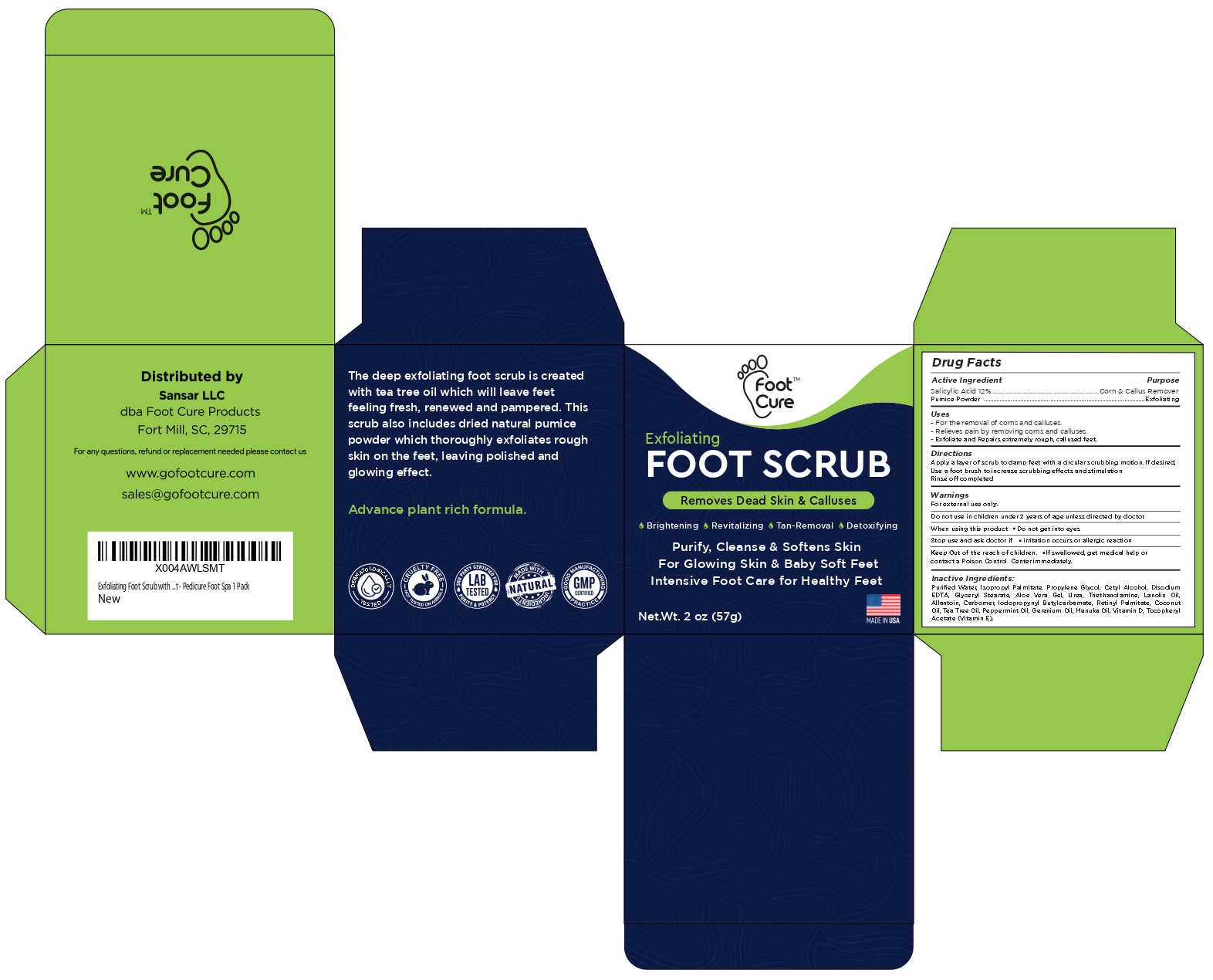 DRUG LABEL: Foot Scrub
NDC: 83691-009 | Form: CREAM
Manufacturer: SANSAR, LLC
Category: otc | Type: HUMAN OTC DRUG LABEL
Date: 20250507

ACTIVE INGREDIENTS: SALICYLIC ACID 12 g/100 g
INACTIVE INGREDIENTS: ISOPROPYL PALMITATE; PROPYLENE GLYCOL; CETYL ALCOHOL; EDETATE DISODIUM; GLYCERYL MONOSTEARATE; ALOE VERA LEAF; UREA; TROLAMINE; LANOLIN OIL; ALLANTOIN; CARBOMER HOMOPOLYMER, UNSPECIFIED TYPE; IODOPROPYNYL BUTYLCARBAMATE; VITAMIN A PALMITATE; COCONUT OIL; TEA TREE OIL; PEPPERMINT OIL; PALMAROSA OIL; MANUKA OIL; VITAMIN D; .ALPHA.-TOCOPHEROL ACETATE

Foot Scrub- Salicylic Acid Corn and Callus Remover

Active ingredient

Salicylic acid 12%

Purpose

Corn and callus remover

Uses

- for the removal of corns and calluses
- Relieves pain by removing corns and calluses
- Exfoliate and Repairs extremely rough, callused feet.

Warnings

For external use only.

Do not use in Children under 2 years of age unless directed by doctor.

When using this product

- Do not get into eyes

Stop use and ask doctor if

- irritation occurs or allergic reaction

KEEP OUT OF REACH OF CHILDREN

Keep out of the reach of children. If swallowed, get medical help or contact a Poison Control Center immediately.

Directions

Apply a layer of scrub to damp feet with a circular scrubbing motion. If desired, Use a foot brush to increase scrubbing effects and stimulation. Rinse off completed

Inactive Ingredients

Purified Water, Isopropyl PaImitate, Propylene Glycol, Cetyl Alcohol, Disodium EDTA, Glyceryl Stearate, Aloe Vera Gel, Urea, Triethanolamine, Lanolin Oil, Allantoin, Carbomer, lodopropynyl Butylcarbamate, Retinyl Palmitate, Coconut Oil, Tea Tree Oil, Peppermint Oil, Geranium Oil, Manuka Oil, Vitamin D, Tocopheryl Acetate (Vitamin E).